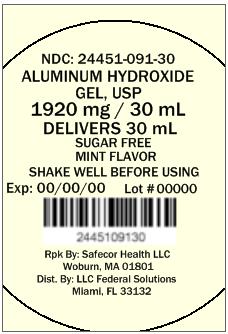 DRUG LABEL: Aluminum Hydroxide
NDC: 24451-091 | Form: GEL
Manufacturer: LLC Federal Solutions
Category: otc | Type: HUMAN OTC DRUG LABEL
Date: 20130812

ACTIVE INGREDIENTS: ALUMINUM HYDROXIDE 320 mg/5 mL
INACTIVE INGREDIENTS: BENZYL ALCOHOL; BUTYLPARABEN; GLYCERIN; HYDROXYETHYL CELLULOSE (4000 MPA.S AT 1%); PROPYLPARABEN; WATER; SACCHARIN SODIUM DIHYDRATE; DIMETHICONE; SORBITOL

Active ingredient (in each 5 mL teaspoonful)
Aluminum hydroxide 320 mg

Purpose
Antacid

Uses
For the relief of

- heartburn
- acid indigestion
- sour stomach

Warnings

Ask a doctor or pharmacist before use if you are taking a prescription drug.
Antacids may interact with certain prescription drugs.

When using this product you may get constipated

Stop use and ask a doctor if symptoms last more than 2 weeks

KEEP OUT OF REACH OF CHILDREN

Keep this and all drugs out of reach of children.

Directions

- shake well before using
- do not take more than 12 teaspoonfuls in 24 hours
- do not use the maximum dosage for more than 2 weeks
- dosage: 2 teaspoonfuls 5-6 times daily after meals and at bedtime followed by a sip of water if needed

Other information

- store at room temperature
- protect from freezing
- keep tightly closed

Inactive ingredients
benzyl alcohol, butylparaben, flavor, glycerin, hydroxyethylcellulose, propylparaben, purified water, saccharin sodium, simethicone emulsion, sorbitol solution

Questions or comments?
Call 1-855-333-6337

Repackaged by:
Safecor Health LLC
317 New Boston St.
Woburn, MA 01801
Distributed by:
LLC Federal Solutions
14 NE 1st Ave.
Miami, FL 33123

PACKAGE LABEL

———PRINCIPAL DISPLAY PANEL———
NDC: 24451-091-30
ALUMINUM HYDROXIDE
GEL, USP
1920 mg / 30 mL
DELIVERS 30 mL
SUGAR FREE
MINT FLAVOR
SHAKE WELL BEFORE USING
Exp: 00/00/00 Lot # 00000
Rpk By: Safecor Health LLC
Woburn, MA 01801
Dist. By: LLC Federal Solutions
Miami, FL 33132